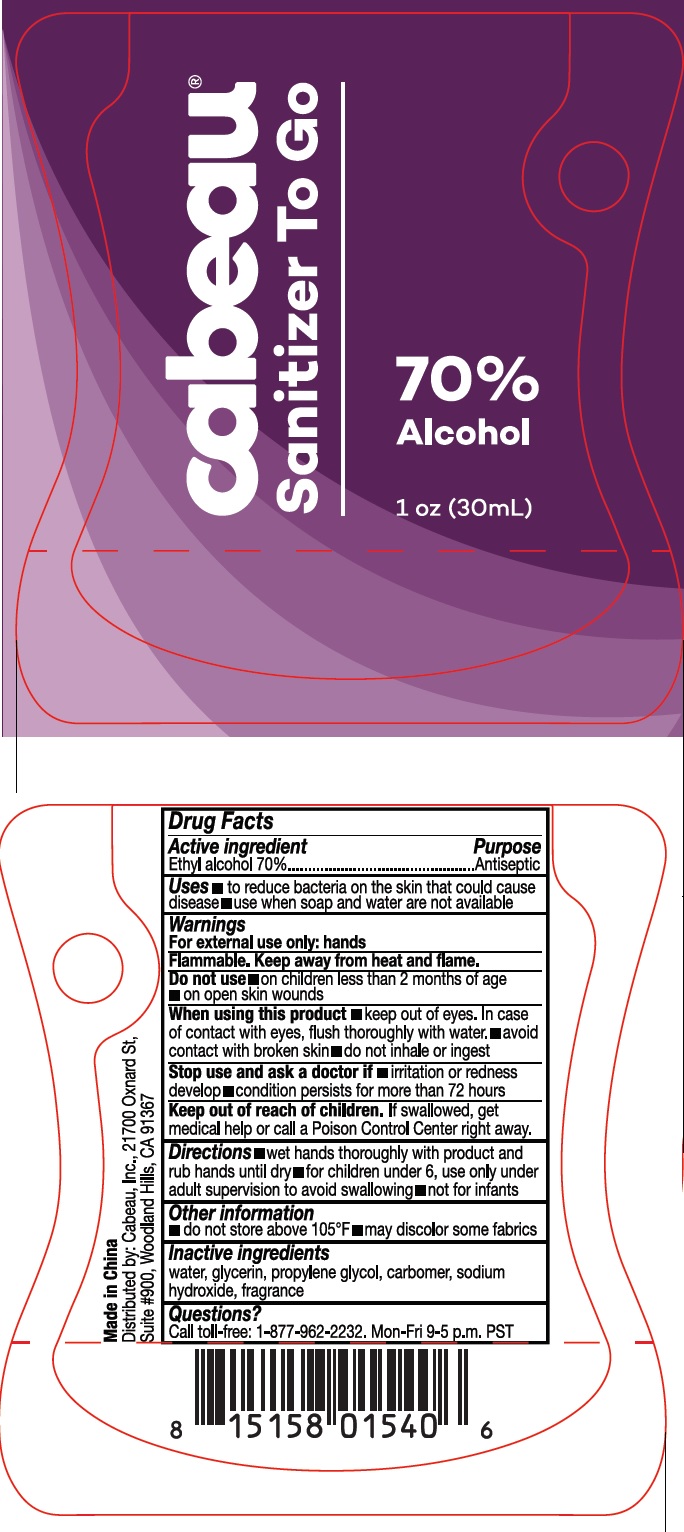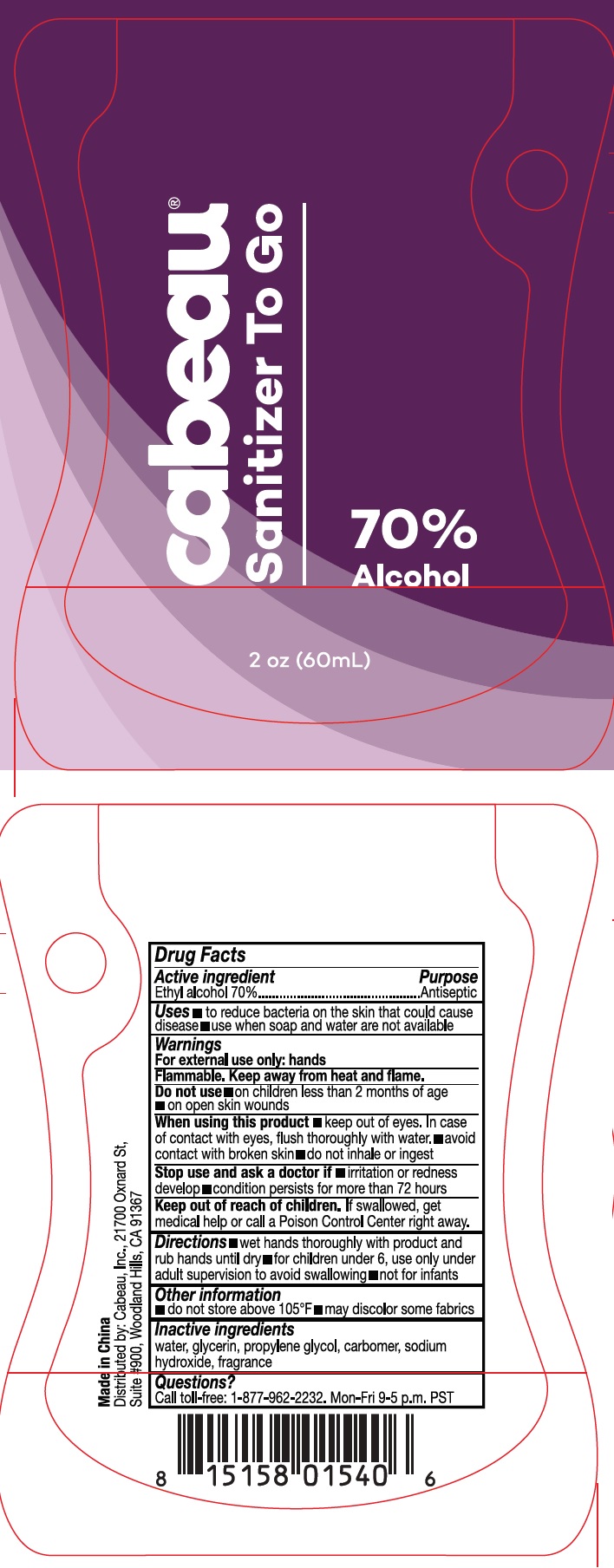 DRUG LABEL: Cabeau Sanitizer To Go
NDC: 77087-001 | Form: LIQUID
Manufacturer: Cabeau Inc.
Category: otc | Type: HUMAN OTC DRUG LABEL
Date: 20200506

ACTIVE INGREDIENTS: ALCOHOL 0.7 mL/1 mL
INACTIVE INGREDIENTS: WATER; GLYCERIN; PROPYLENE GLYCOL; CARBOMER HOMOPOLYMER, UNSPECIFIED TYPE; SODIUM HYDROXIDE

Cabeau Sanitizer To Go

Active ingredient

Ethyl alcohol 70%

Purpose

Antiseptic

Uses

- to reduce bacteria on the skin that could cause disease
- use when soap and water are not available

Warnings

For external use only: hands

Flammable. Keep away from heat and flame.

Do not use

- on children less than 2 months of age
- on open skin wounds

When using this product

- keep out of eyes. In case of contact with eyes, flush thoroughly with water.
- avoid contact with broken skin
- do not inhale or ingest

Stop use and ask a doctor if

- irritation or redness develop
- condition persists for more than 72 hours

Keep out of reach of children.

If swallowed, get medical help or call a Poison Control Center right away.

Directions

- wet hands thoroughly with product and rub hands unitl dry
- for children under 6, use only under adult supervision to avoid swallowing
- not for infants

Other information

- do not store above 105°F
- may discolor some fabrics

Inactive ingredients

water, glycerin, propylene glycol, carbomer, sodium hydroxide, fragrace

Questions?

Call toll-free: 1-877-962-2232. Mon-Fri 9-5 p.m. PST